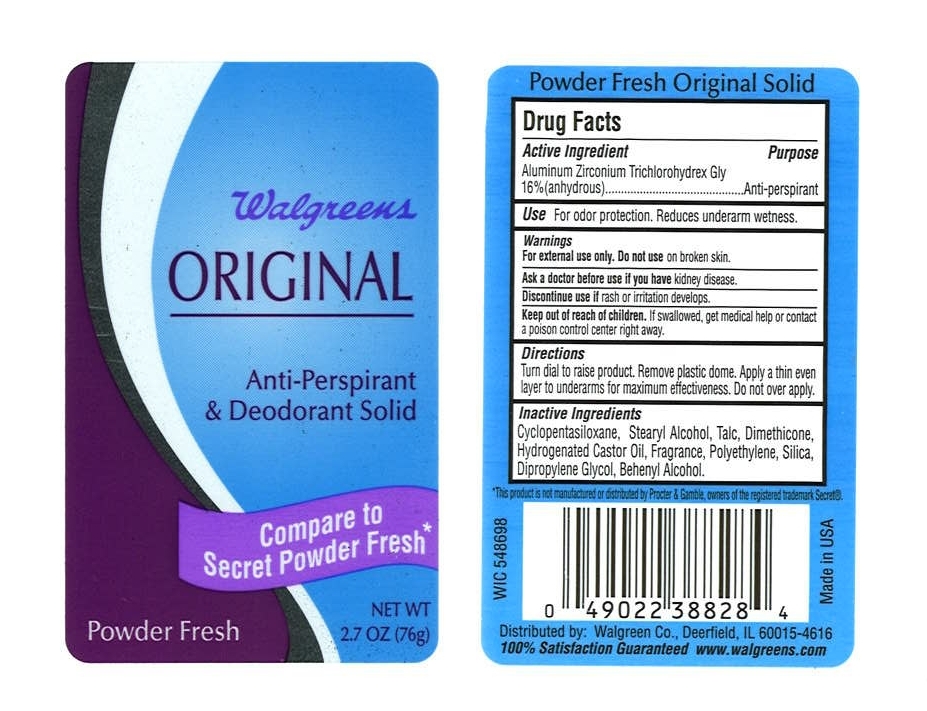 DRUG LABEL: Walgreens Original
NDC: 10889-105 | Form: STICK
Manufacturer: VVF Kansas Services LLC
Category: otc | Type: HUMAN OTC DRUG LABEL
Date: 20091023

ACTIVE INGREDIENTS: aluminum zirconium tetrachlorohydrex gly 16.0 1/1 1

Walgreens Original Powder Fresh (Aluminun Zirconium Tetrachlorohydrex Gly)

ACTIVE INGREDIENT

Aluminum Zirconium Tetrachlorohydrex Gly (anhydrous) 16%

PURPOSE

Anti-perspirant

USES

For odor protection. Reduces underarm wetness.

Turn dial to raise product. Remove plastic dome. Apply a thin even layer to underarms for maximum effectiveness. Do not over apply.

WARNINGS

For external use only. Do not use on broken skin.

Ask a doctor before you use if you have kidney disease.

Discontinue use if rash or irritation develops.

Keep out of reach of children. If swallowed, get medical help or contact a poison control center right away.

INACTIVE INGREDIENTS

Cyclopentasiloxane, Stearyl Alcohol, Talc, Dimethicone, Hydrogenated Castor Oil, Fragrance, Polyethylene, Silica, Dipropylene Glycol, Behenyl Alcohol.

* This product is not manufactured or distributed by Proctor and Gamble, owners of the registered trademark Secret (R).
Distributed by:
Walgreen Co., Deerfield, IL 60015-4616
100% Satisfaction Guaranteed www.walgreens.com
Made in USA
WIC 548698

PRODUCT LABEL

Walgreens ORIGINAL

Anti-Perspirant and Deodorant Solid

Compare to Secret Powder Fresh*

Powder Fresh

NET WT. 2.7 OZ. (76g)